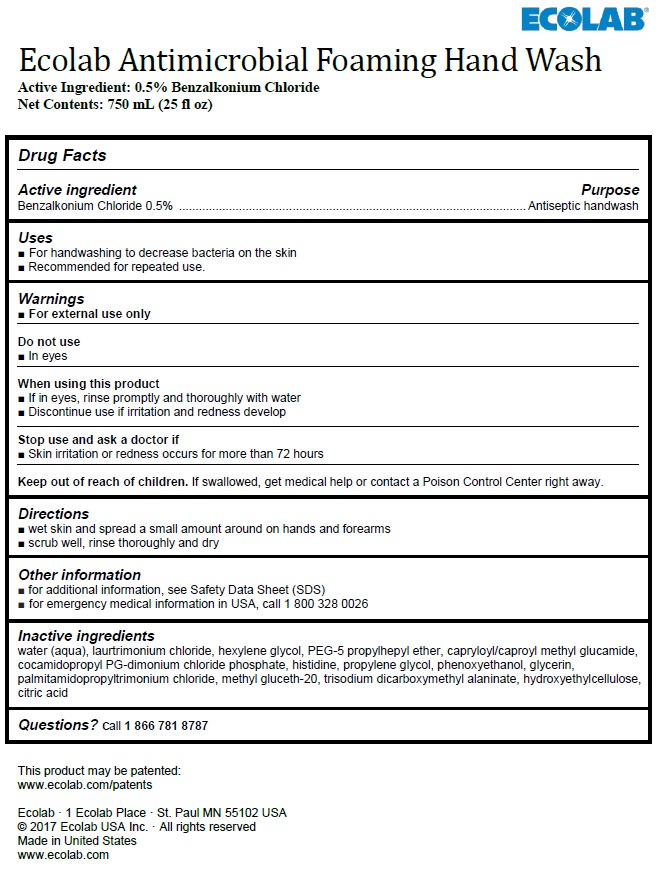 DRUG LABEL: Ecolab
NDC: 47593-613 | Form: SOLUTION
Manufacturer: Ecolab Inc.
Category: otc | Type: HUMAN OTC DRUG LABEL
Date: 20240805

ACTIVE INGREDIENTS: BENZALKONIUM CHLORIDE 5 mg/1 mL
INACTIVE INGREDIENTS: WATER; LAURTRIMONIUM CHLORIDE; HEXYLENE GLYCOL; PEG-5 PROPYLHEPTYL ETHER; CAPRYLOYL/CAPROYL METHYL GLUCAMIDE; COCAMIDOPROPYL PROPYLENE GLYCOL-DIMONIUM CHLORIDE PHOSPHATE; HISTIDINE; PROPYLENE GLYCOL; PHENOXYETHANOL; GLYCERIN; PALMITAMIDOPROPYLTRIMONIUM CHLORIDE; METHYL GLUCETH-20; TRISODIUM DICARBOXYMETHYL ALANINATE; HYDROXYETHYL CELLULOSE (2000 MPA.S AT 1%); ANHYDROUS CITRIC ACID

Drug Facts

Active ingredient

Benzalkonium Chloride, 0.5%

Purpose

Antiseptic handwash

Uses

- For handwashing to decrease bacteria on the skin
- Recommended for repeated use.

Warnings

- For external use only

Do not use

- In eyes

When using this product

- If in eyes, rinse promptly and thoroughly with water
- Discontinue use if irritation and redness develop

Stop use and ask a doctor if

- Skin irritation or redness occurs for more than 72 hours

Keep out of reach of children. If swallowed, get medical help or contact a Poison Control Center right away.

Directions

- wet skin and spread a small amount around on hands and forearms
- scrub well, rinse thoroughly and dry

Other information

- for additional information, see Safety Data Sheet (SDS)
- for emergency medical information in USA, call 1 800 328 0026

Inactive ingredients

water (aqua), laurtrimonium chloride, hexylene glycol, PEG-5 propylhepyl ether, capryloyl/caproyl methyl glucamide, cocamidopropyl PG-dimonium chloride phosphate, histidine, propylene glycol, phenoxyethanol, glycerin, palmitamidopropyltrimonium chloride, methyl gluceth-20, trisodium dicarboxymethyl alaninate, hydroxyethylcellulose, citric acid

Questions? call 1 866 781 8787

Prinicpal Display Panel / Representative Label

Ecolab Antimicrobial Foaming Hand Wash

Active Ingredient: 0.5% Benzalkonium Chloride
Net Contents: 750 mL (25 fl oz)

This product may be patented:
www.ecolab.com/patents

Ecolab · 1 Ecolab Place · St. Paul MN 55102 USA
© 2017 Ecolab USA Inc. · All rights reserved
Made in United States
www.ecolab.com